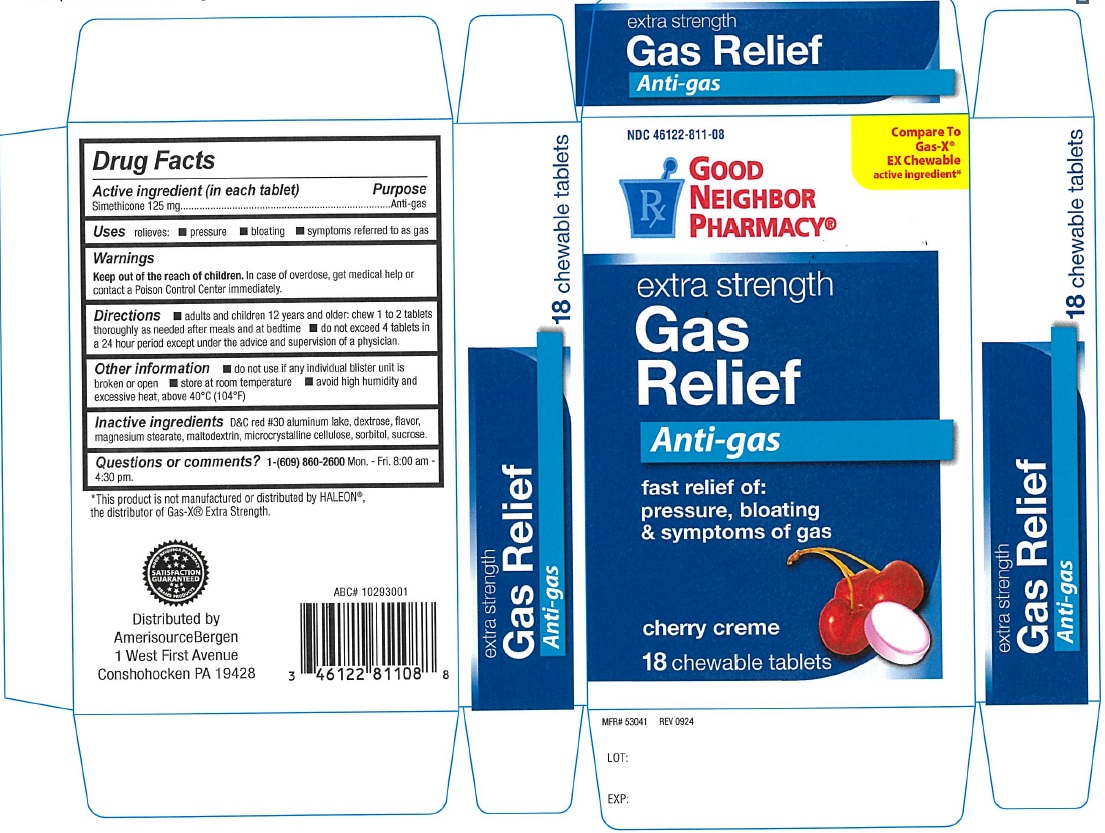 DRUG LABEL: extra strength Gas Relief cherry creme
NDC: 46122-811 | Form: TABLET, CHEWABLE
Manufacturer: Amerisource Bergen
Category: otc | Type: Human OTC Drug Label
Date: 20250108

ACTIVE INGREDIENTS: DIMETHICONE 125 mg/1 1
INACTIVE INGREDIENTS: D&C RED NO. 30 ALUMINUM LAKE; MAGNESIUM STEARATE; CELLULOSE, MICROCRYSTALLINE; SORBITOL; SUCROSE; MALTODEXTRIN; DEXTROSE, UNSPECIFIED FORM

GNP extra strength Gas Relief 134CHR

ACTIVE INGREDIENT(S)

Simethicone 125 mg

PURPOSE

Anti-gas

USE(S)

relieves:

- Pressure
- bloating
- Symptoms referred to as gas

WARNINGS

.

KEEP OUT OF THE REACH OF CHILDREN.

In case of overdose, get medical help or contact a Poison Control Centre immediately.

DIRECTIONS

- adults and children 12 years and older: chew 1 to 2 tablets thoroughly as needed after meals and at bedtime
- do not exceed 4 tablets in a 24 hour period except under the advice and supervision of a physician.

OTHER INFORMATION

- do not use if any individual blister unit is broken or open
- store at room temperature
- avoid high humidity and excessive heat, above 40ºC (104ºF)

INACTIVE INGREDIENTS

D&C red #30 aluminum lake, dextrose, flavor, magnesium stearate, maltodextrin, microcrystalline cellulose, sorbitol, sucrose.

Questions or comments?

1-(609) 860-2600 Mon. - Fri. 8:00 am - 4:30 pm.

PRINCIPAL DISPLAY PANEL

NDC 46122-811-08

GOOD NEIGHBOR PHARMACY®

Compare To Gas-X®

EX Chewable active ingredient*

extra strength

Gas Relief

Anti-gas

fast relief of:

pressure, bloating

& symptoms of gas

cherry creme

18 chewable tablets